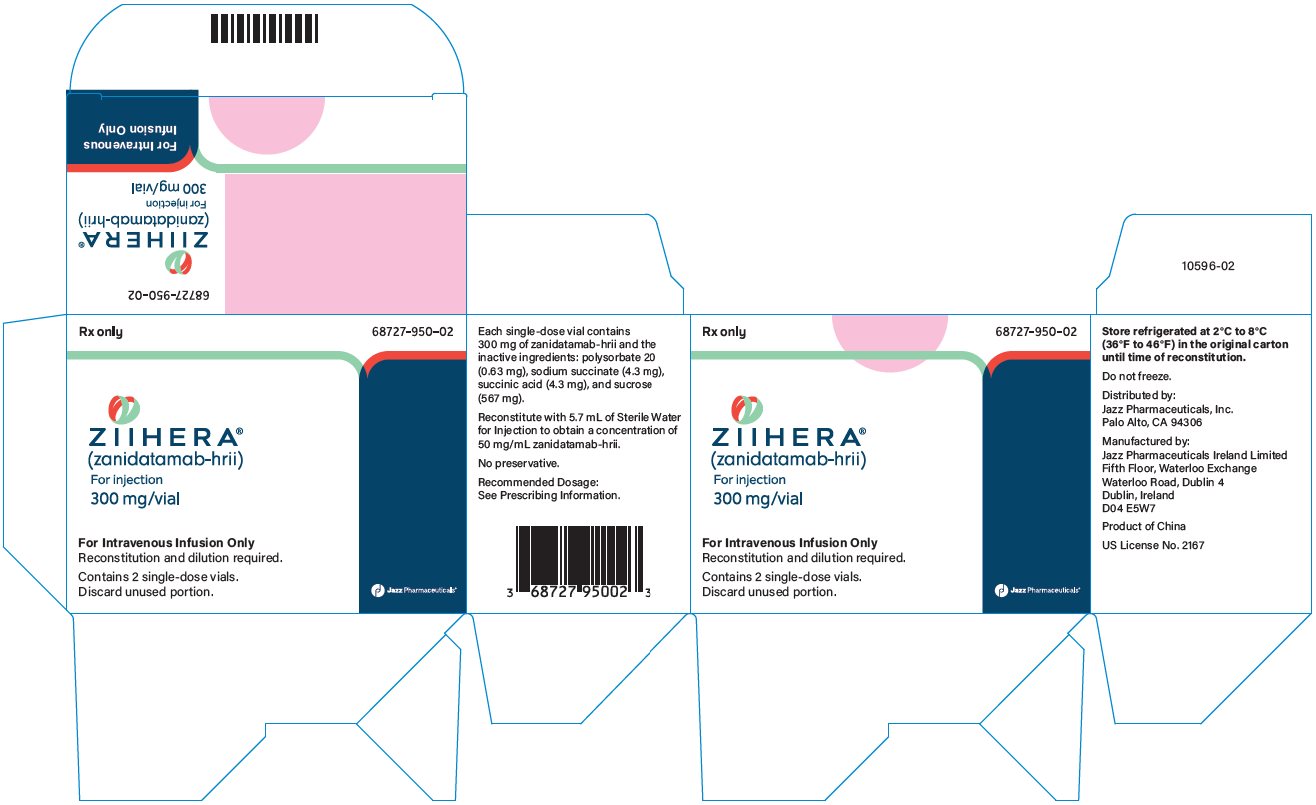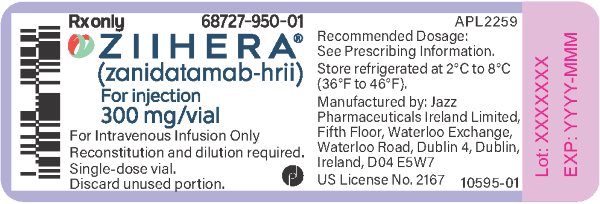 DRUG LABEL: ZIIHERA
NDC: 68727-950 | Form: INJECTION, POWDER, LYOPHILIZED, FOR SOLUTION
Manufacturer: Jazz Pharmaceuticals, Inc.
Category: prescription | Type: HUMAN PRESCRIPTION DRUG LABEL
Date: 20250701

ACTIVE INGREDIENTS: ZANIDATAMAB 50 mg/1 mL
INACTIVE INGREDIENTS: SODIUM SUCCINATE ANHYDROUS 4.3 mg/1 mL; POLYSORBATE 20 0.63 mg/1 mL; SUCCINIC ACID 4.3 mg/1 mL; SUCROSE 567 mg/1 mL

HIGHLIGHTS OF PRESCRIBING INFORMATION

These highlights do not include all the information needed to use ZIIHERA safely and effectively. See full prescribing information for ZIIHERA.
ZIIHERA® (zanidatamab‑hrii) for injection, for intravenous use.
Initial U.S. Approval: 2024

WARNING: EMBRYO-FETAL TOXICITY

See full prescribing information for complete boxed warning.

- Exposure to ZIIHERA during pregnancy can cause embryo-fetal harm. Advise patients of the risk and need for effective contraception. (5.1)

1 INDICATIONS AND USAGE

ZIIHERA is a bispecific HER2-directed antibody indicated for the treatment of adults with previously treated, unresectable or metastatic HER2-positive (IHC 3+) biliary tract cancer (BTC), as detected by an FDA-approved test. (1)

This indication is approved under accelerated approval based on overall response rate and duration of response. Continued approval for this indication may be contingent upon verification and description of clinical benefit in a confirmatory trial(s). (1)

2 DOSAGE AND ADMINISTRATION

- Premedicate patients with acetaminophen, an antihistamine and a corticosteroid, 30‑60 minutes prior to each administration of ZIIHERA infusion to prevent potential infusion-related reactions (IRRs). (2.2)
- The recommended dosage of ZIIHERA is 20 mg/kg given as an intravenous infusion once every 2 weeks. (2.3)

3 DOSAGE FORMS AND STRENGTHS

For injection: 300 mg lyophilized powder in a single-dose vial. (3)

4 CONTRAINDICATIONS

- None. (4)

5 WARNINGS AND PRECAUTIONS

- Left Ventricular Dysfunction: Assess left ventricular ejection fraction (LVEF) prior to initiation of ZIIHERA and at regular intervals during treatment. Withhold or permanently discontinue ZIIHERA based on severity. (2.4, 5.2)
- Infusion-Related Reactions (IRRs): Premedicate before each infusion of ZIIHERA. Interrupt the infusion, decrease the infusion rate, and/or permanently discontinue ZIIHERA based on severity. (2.4, 5.3)
- Diarrhea: ZIIHERA can cause severe diarrhea. Administer antidiarrheal treatment as clinically indicated. Withhold or permanently discontinue ZIIHERA based on severity. (2.4, 5.4)

6 ADVERSE REACTIONS

Most common adverse reactions (≥ 20%) are diarrhea, infusion-related reaction, abdominal pain, and fatigue. (6.1)

To report SUSPECTED ADVERSE REACTIONS, contact Jazz Pharmaceuticals, Inc. at 1‑800‑520‑5568 or FDA at 1-800-FDA-1088 or www.fda.gov/medwatch.

8 USE IN SPECIFIC POPULATIONS

- Females and Males of Reproductive Potential: Verify the pregnancy status of females prior to initiation of ZIIHERA. (8.3)

FULL PRESCRIBING INFORMATION

WARNING: EMBRYO-FETAL TOXICITY

Embryo-Fetal Toxicity: Exposure to ZIIHERA during pregnancy can cause embryo-fetal harm. Advise patients of the risk and need for effective contraception [see Warnings and Precautions (5.1), Use in Specific Populations (8.1, 8.3)].

1 INDICATIONS AND USAGE

ZIIHERA is indicated for the treatment of adults with previously treated, unresectable or metastatic HER2-positive (IHC 3+) biliary tract cancer (BTC), as detected by an FDA-approved test [see Dosage and Administration (2.1)].

This indication is approved under accelerated approval based on overall response rate and duration of response [see Clinical Studies (14)]. Continued approval for this indication may be contingent upon verification and description of clinical benefit in a confirmatory trial(s).

2 DOSAGE AND ADMINISTRATION

2.1 Patient Selection

Select patients for treatment of unresectable or metastatic biliary tract cancer based on HER2-positive (IHC 3+) tumor specimens, as detected by an FDA-approved test [see Clinical Studies (14)].

Information on FDA-approved tests for HER2 protein expression in biliary tract cancers is available at: http://www.fda.gov/CompanionDiagnostics.

2.2 Premedications

Premedicate all patients 30 to 60 minutes prior to each dose of ZIIHERA to reduce the risk of infusion-related reactions [see Warnings and Precautions (5.3)]:

- Administer acetaminophen, an antihistamine (such as diphenhydramine) and a corticosteroid (such as hydrocortisone).

2.3 Recommended Dosage

Recommended Dosage and Administration

The recommended dosage of ZIIHERA is 20 mg/kg, administered as an intravenous infusion once every 2 weeks until disease progression or unacceptable toxicity.

Missed dose

If a planned dose of ZIIHERA is delayed or missed, administer the dose as soon as possible; do not wait until the next planned dose. Adjust the administration schedule to maintain a 2-week interval between doses.

2.4 Dosage Modifications for Adverse Reactions

- The recommended dosage reduction of ZIIHERA for adverse reactions is 15 mg/kg as described in Table 1.
- Permanently discontinue ZIIHERA in patients who cannot tolerate 15 mg/kg.

Table 1 Dosage Modifications for Adverse Reactions
Adverse Reaction | Severity | Treatment Modification
Left Ventricular Dysfunction (LVD); [see Warnings and Precautions (5.2)] | Absolute decrease of ≥ 16% points in LVEF from pre-treatment baseline; or; LVEF ≤ 50% and absolute decrease of ≥ 10% points below pre-treatment baseline | - Withhold ZIIHERA for at least 4 weeks. - Repeat LVEF assessment within 4 weeks. - Resume ZIIHERA treatment within 4 to 8 weeks if LVEF returns to normal limits and the absolute decrease is ≤ 15% points from baseline. - Permanently discontinue ZIIHERA if LVEF has not recovered to within 15% points from pre-treatment baseline.
Left Ventricular Dysfunction (LVD); [see Warnings and Precautions (5.2)] | Confirmed symptomatic congestive heart failure | - Permanently discontinue ZIIHERA.
Infusion-Related Reactions; [see Warnings and Precautions (5.3)] | Mild (Grade 1) | - Reduce ZIIHERA infusion rate by 50%. - For subsequent ZIIHERA infusions increase infusion rate gradually to the rate prior to the adverse reaction, as tolerated.
Infusion-Related Reactions; [see Warnings and Precautions (5.3)] | Moderate (Grade 2) | - Stop ZIIHERA infusion immediately. - Treat with appropriate therapy. - Resume ZIIHERA infusion at 50% of previous infusion rate once symptoms resolve. - For subsequent ZIIHERA infusions increase infusion rate gradually to the rate prior to the adverse reaction, as tolerated.
Infusion-Related Reactions; [see Warnings and Precautions (5.3)] | Severe (Grade 3) | - Stop ZIIHERA infusion immediately. - Promptly treat with appropriate therapy; infusion should not be restarted during the same cycle even if signs and symptoms completely resolve. - Subsequent ZIIHERA infusions should be administered at 50% of previous infusion rate. - Permanently discontinue ZIIHERA for recurrent Grade 3 reaction.
Infusion-Related Reactions; [see Warnings and Precautions (5.3)] | Life threatening (Grade 4) | - Stop ZIIHERA infusion immediately and permanently discontinue. - Promptly treat with appropriate therapy.
Diarrhea; [see Warnings and Precautions (5.4)] | Mild/Moderate (Grade 1 or 2) | - No dose modification of ZIIHERA is required. - Initiate appropriate medical therapy and monitor as clinically indicated.
Diarrhea; [see Warnings and Precautions (5.4)] | Severe (Grade 3) | - Withhold ZIIHERA treatment until severity improves to ≤ Grade 1. - Initiate or intensify appropriate medical therapy and monitor as clinically indicated. - Administer subsequent ZIIHERA treatment at the same dose level or consider dose reduction to 15 mg/kg. - For recurrent Grade 3 symptoms, withhold ZIIHERA treatment and ensure medical management has been optimized. - Resume ZIIHERA treatment at a reduced dose of 15 mg/kg after severity improves to ≤ Grade 1. - Permanently discontinue ZIIHERA for recurrent Grade 3 symptoms that last > 3 days despite optimized medical management.
Diarrhea; [see Warnings and Precautions (5.4)] | Life threatening (Grade 4) | - Permanently discontinue ZIIHERA
Pneumonitis; [see Adverse Reactions (6.1)] | Confirmed Grade ≥ 2 | - Permanently discontinue ZIIHERA.
Other Adverse Reactions (excluding LVD, IRR, Diarrhea, and Pneumonitis); [see Adverse Reactions (6.1)] | Mild/Moderate (Grades 1/2) | - No dosage modification is required for ZIIHERA. - Initiate appropriate medical therapy and monitor as clinically indicated.
Other Adverse Reactions (excluding LVD, IRR, Diarrhea, and Pneumonitis); [see Adverse Reactions (6.1)] | Severe (Grade 3) | - Withhold ZIIHERA treatment until severity improves to ≤ Grade 1. - Initiate appropriate medical therapy and monitor as clinically indicated. - Administer subsequent ZIIHERA treatment at the same dose; consider dose reduction to 15 mg/kg if Grade 3 symptoms recur.
Other Adverse Reactions (excluding LVD, IRR, Diarrhea, and Pneumonitis); [see Adverse Reactions (6.1)] | Life Threatening (Grade 4) | - Permanently discontinue ZIIHERA, except as noted below. - Initiate appropriate medical therapy and monitor as clinically indicated. - ZIIHERA treatment may be resumed at the same dose level for Grade 4 electrolyte imbalances or laboratory abnormalities that are corrected within 3 days of onset; do not resume until symptoms improve to ≤ Grade 1. - Permanently discontinue ZIIHERA for recurrent Grade 4 electrolyte imbalances or laboratory abnormalities.

2.5 Preparation and Administration Instructions

Administer only as an intravenous infusion after ZIIHERA is reconstituted and diluted.

Reconstitution

- Calculate the recommended dose based on the patient’s weight to determine the number of vials needed.
- Remove the vial(s) from the refrigerator and allow the vial(s) to reach room temperature.
- Reconstitute each 300 mg vial of ZIIHERA with 5.7 mL of Sterile Water for Injection by slowly directing the stream toward the inside of the wall of the vial, to obtain a final concentration of 50 mg/mL in an extractable volume of 6 mL.
- Swirl the vial gently until completely dissolved. Do not shake or vigorously swirl.
- Allow the reconstituted vial to settle to allow bubbles to dissipate.
- Parenteral drug products should be inspected visually for particulate matter and discoloration prior to administration, whenever solution and container permit. The reconstituted product should be a colorless to light yellow, clear to slightly opalescent solution with no visible particles. Discard the reconstituted vial if any discoloration or particulate matter is observed.
- The product does not contain a preservative. Use the reconstituted ZIIHERA solution immediately or store the reconstituted ZIIHERA solution for up to 4 hours, either at room temperature (18°C to 24°C [64°F to 75°F]) or in a refrigerator (2°C to 8ºC [36°F to 46ºF]).

Dilution

- Withdraw the necessary volume for the calculated dose from each vial [see Dosage and Administration (2.3)].
- Slowly add the necessary dose volume to an infusion bag containing 0.9% Sodium Chloride Injection or 5% Dextrose Injection to prepare an infusion solution with a final concentration of the diluted solution between 0.4 mg/mL and 6 mg/mL.
- Gently invert the infusion bag to mix. Do not shake.
- The infusion solution must be a clear, colorless solution with no visible particles. Do not use if visible particles are observed or if the solution is discolored.
- Discard any unused portion left in the vial(s).
- Use the infusion solution immediately upon dilution or store the infusion solution at room temperature (18°C to 24°C [64°F to 75°F]) for up to 12 hours or in the refrigerator (2ºC to 8ºC [36ºF to 46ºF]) for up to 24 hours.
  - These time limits include the beginning of reconstitution through the duration of infusion.
  - If these specified times are exceeded, discontinue the current infusion bag and prepare a new bag which contains the remaining dosage of ZIIHERA to be infused.
- Compatibility with intravenous administration materials and the infusion solution has been demonstrated in the following materials:
  - Intravenous (IV) Bag: Polyvinyl chloride (PVC), polyolefin (PO), ethyl vinyl acetate (EVA), polypropylene (PP) and ethylene-propylene copolymer.
  - Infusion sets: Polyvinyl chloride/ bis (2-ethylhexyl) phthalate (PVC/DEHP). Polyurethane (PUR), polyethylene-lined (PE-lined) acrylonitrile-butadiene-styrene (ABS).
  - Inline filters: Polyethersulfone solution filter (PES), polyvinylidene fluoride air filter (PVDF).
  - Closed System Transfer devices: acrylonitrile-butadiene-styrene (ABS), acrylic c-polymer, polycarbonate (PC), polyisoprene (PI), polyester, polypropylene (PP) polytetrafluoroethylene (PTFE), silicone and stainless steel (SS).

Administration

- Administer ZIIHERA as an intravenous infusion with a 0.2 or 0.22 micron filter.
- Do not administer as an intravenous push or bolus.
- Do not co-administer ZIIHERA and other intravenous drugs through the same intravenous line.

Table 2: Recommended ZIIHERA Infusion Durations
Dose | Infusion Duration
First and Second | 120-150 minutes
Third and Fourth | 90 minutes, if previous infusions were well-tolerated
Subsequent | 60 minutes, if previous infusions were well-tolerated

3 DOSAGE FORMS AND STRENGTHS

For injection: 300 mg white lyophilized powder in a single-dose vial.

4 CONTRAINDICATIONS

None.

5 WARNINGS AND PRECAUTIONS

5.1 Embryo-Fetal Toxicity

Based on the mechanism of action, ZIIHERA can cause fetal harm when administered to a pregnant woman. There are no human or animal data on the use of ZIIHERA in pregnancy. In literature reports, use of a HER2-directed antibody during pregnancy resulted in cases of oligohydramnios and oligohydramnios sequence manifesting as pulmonary hypoplasia, skeletal abnormalities, and neonatal death.

Verify the pregnancy status of females of reproductive potential prior to the initiation of ZIIHERA. Advise pregnant women and females of reproductive potential that exposure to ZIIHERA during pregnancy or within 4 months prior to conception can result in fetal harm. Advise females of reproductive potential to use effective contraception while receiving ZIIHERA and for 4 months following the last dose of ZIIHERA.

5.2 Left Ventricular Dysfunction

ZIIHERA can cause decreases in left ventricular ejection fraction (LVEF). LVEF declined by greater than 10% and decreased to less than 50% in 4.3% of 233 patients. LVD leading to permanent discontinuation of ZIIHERA was reported in 0.9% of patients. The median time to first occurrence of left ventricular dysfunction was 5.6 months (range: 1.6 to 18.7 months). Left ventricular dysfunction resolved in 70% of patients.

Assess LVEF prior to initiation of ZIIHERA and at regular intervals during treatment. Withhold dose or permanently discontinue ZIIHERA based on severity of adverse reactions [see Dosage and Administration (2.4)].

The safety of ZIIHERA has not been established in patients with a baseline ejection fraction that is below 50% [see Dosage and Administration (2.4)].

5.3 Infusion-Related Reactions

ZIIHERA can cause infusion-related reactions (IRRs). An IRR was reported in 31% of 233 patients treated with ZIIHERA as a single agent in clinical studies, including Grade 3 (0.4%), and Grade 2 (25%). IRRs leading to permanent discontinuation of ZIIHERA were reported in 0.4% of patients. IRRs occurred on the first day of dosing in 28% of patients; 97% of IRRs resolved within one day.

Prior to each dose of ZIIHERA, administer premedications to prevent potential IRRs [see Dosage and Administration (2.2)]. Monitor patients for signs and symptoms of IRR during ZIIHERA administration and as clinically indicated after completion of infusion. Have medications and emergency equipment to treat IRRs available for immediate use.

If an IRR occurs, slow, or stop the infusion, and administer appropriate medical management. Monitor patients until complete resolution of signs and symptoms before resuming. Permanently discontinue ZIIHERA in patients with recurrent severe or life-threatening infusion-related reactions [see Dosage and Administration (2.4)].

5.4 Diarrhea

ZIIHERA can cause severe diarrhea [see Adverse Reactions (6.1)].

Diarrhea was reported in 48% of 233 patients treated in clinical studies, including Grade 3 (6%) and Grade 2 (17%). If diarrhea occurs, administer antidiarrheal treatment as clinically indicated. Perform diagnostic tests as clinically indicated to exclude other causes of diarrhea. Withhold or permanently discontinue ZIIHERA based on severity [see Dosage and Administration (2.4)].

6 ADVERSE REACTIONS

The following clinically significant adverse reactions are described in greater detail in other sections of the labeling:

- Embyro-Fetal Toxicity [see Warnings and Precautions (5.1)]
- Left Ventricular dysfunction [see Warnings and Precautions (5.2)]
- Infusion-Related Reactions [see Warnings and Precautions (5.3)]
- Diarrhea [see Warnings and Precautions (5.4)]

6.1 Clinical Trials Experience

Because clinical trials are conducted under widely varying conditions, adverse reaction rates observed in the clinical trials of a drug cannot be directly compared to rates in the clinical trials of another drug and may not reflect the rates observed in practice.

The pooled safety population of ZIIHERA described in WARNINGS AND PRECAUTIONS reflect exposure in 233 patients administered ZIIHERA 20 mg/kg intravenously as a single agent in two single-arm, open-label studies (ZWI‑ZW25‑101 and HERIZON‑BTC‑01), which enrolled 109 patients with biliary tract cancer, and 124 patients with other cancers. Among 233 patients who received ZIIHERA, 39% were exposed for 6 months or longer, and 17% were exposed for greater than one year.

Biliary Tract Cancer

The safety of ZIIHERA was evaluated in 80 patients with previously treated, unresectable or metastatic HER2-positive biliary tract cancer who received at least one prior gemcitabine-containing chemotherapy regimen in HERIZON‑BTC‑01 [See Clinical Studies (14)]. Patients received ZIIHERA 20 mg/kg by IV infusion once every 2 weeks until disease progression or unacceptable toxicity. The median duration of exposure to ZIIHERA was 5.6 months (range: 0.5 to 27.2 months).

Serious adverse reactions occurred in 53% of patients who received ZIIHERA. Serious adverse reactions in > 2% of patients included biliary obstruction (15%), biliary tract infection (8%), sepsis (8%), pneumonia (5%), diarrhea (3.8%), gastric obstruction (3.8%), and fatigue (2.5%). A fatal adverse reaction of hepatic failure occurred in one patient who received ZIIHERA.

Permanent discontinuation due to an adverse reaction occurred in 2.5% of patients who received ZIIHERA. Adverse reactions which resulted in permanent discontinuation in ≥ 1% of patients who received ZIIHERA included decreased ejection fraction and pneumonitis.

Dosage interruptions due to an adverse reaction, excluding temporary interruptions of ZIIHERA infusions due to infusion-related reactions, occurred in 41% of patients who received ZIIHERA. The most frequent adverse reactions (> 2% of patients) that required dosage interruption were diarrhea, increased alanine aminotransferase, increased aspartate aminotransferase, decreased ejection fraction, pneumonia, cholangitis, fatigue, biliary obstruction, abdominal pain, increased blood creatinine, and decreased potassium.

Dosage reductions due to an adverse reaction occurred in 4% of patients who received ZIIHERA. Adverse reactions requiring dosage reductions in > 1% of patients were diarrhea, nausea, and decreased weight.

The most common adverse reactions in patients receiving ZIIHERA (≥ 20%) were diarrhea, infusion-related reaction, abdominal pain, and fatigue.

Table 3 summarizes the adverse reactions that occurred in HERIZON‑BTC‑01.

Table 3: Adverse Reactions (≥ 15%) in Patients with Unresectable or Metastatic HER2-Positive BTC Receiving ZIIHERA in HERIZON-BTC-01
Adverse Reaction* | ZIIHERA N=80
 | All Grades (%) | Grades 3 or 4 (%)
Gastrointestinal disorders
Diarrheaa | 50 | 10
Abdominal painb | 29 | 1
Nausea | 18 | 1
Vomiting | 15 | 1
Injury, poisoning and procedural complications
Infusion-related reaction | 35 | 1
General disorders and administration site conditions
Fatiguec | 24 | 4
Skin and subcutaneous tissue disorders
Rashd | 19 | 0
Metabolism and nutrition disorders
Decreased appetite | 16 | 0

* Graded per CTCAE version 5.

a Diarrhea includes diarrhea and enteritis

b Abdominal pain includes abdominal pain and abdominal pain upper

c Fatigue includes asthenia and fatigue

d Rash includes dermatitis, dermatitis acneiform, palmar-plantar erythrodysaesthesia syndrome, rash, rash maculo-papular, and rash pustular

Table 4 summarizes the laboratory abnormalities in HERIZON‑BTC‑01.

Table 4: Laboratory Abnormalities (≥ 30%) that Worsened from Baseline in Patients with Unresectable or Metastatic HER2-Positive BTC Receiving ZIIHERA in HERIZON-BTC-01
Laboratory Abnormalities | ZIIHERA*
 | All Grades (%) | Grades 3 or 4 (%)
Hematology
Hemoglobin decreased | 88 | 14
Lymphocytes decreased | 44 | 8
Chemistry
Lactate dehydrogenase increased | 55 | 0
Albumin decreased | 53 | 0
Aspartate aminotransferase increased | 47 | 10
Alanine aminotransferase increased | 46 | 8
Alkaline phosphatase increased | 41 | 5
Sodium decreased | 35 | 10
Potassium decreased | 34 | 5

*The denominator used to calculate the rate varied from 78 to 80 based on the number of patients with a baseline value and at least one post-treatment value.

8 USE IN SPECIFIC POPULATIONS

8.1 Pregnancy

Risk Summary

Based on mechanism of action, ZIIHERA can cause fetal harm when administered to a pregnant woman. There are no human or animal data on the use of ZIIHERA in pregnancy. In literature reports, use of a HER2-directed antibody during pregnancy resulted in cases of oligohydramnios and oligohydramnios sequence manifesting as pulmonary hypoplasia, skeletal abnormalities, and neonatal death. Use of ZIIHERA is not recommended during pregnancy (see CLINICAL CONSIDERATIONS). Advise patients of potential risks to a fetus.

The estimated background risk of major birth defects and miscarriage for the indicated population is unknown. All pregnancies have a background risk of birth defect, loss, or other adverse outcomes. In the U.S. general population, background risks of major birth defects and miscarriage in clinically recognized pregnancies are 2 to 4% and 15 to 20%, respectively.

Clinical Considerations

Fetal/Neonatal Adverse Reactions

Monitor women who received ZIIHERA during pregnancy or within 4 months prior to conception for oligohydramnios. If oligohydramnios occurs, perform fetal testing that is appropriate for gestational age and consistent with local standard of care.

8.2 Lactation

Risk Summary

There are no data on the presence of zanidatamab‑hrii in human milk, the effects on the breastfed child, or the effects on milk production. Published data suggest human IgG is present in human milk but does not enter neonatal or infant circulation in substantial amounts. Consider developmental and health benefits of breastfeeding along with the mother’s clinical need for ZIIHERA treatment and any potential adverse effects on the breastfed child from ZIIHERA or from the underlying maternal condition. This consideration should also take into account the ZIIHERA half-life of approximately 21 days and a washout period of 4 months [see Clinical Pharmacology (12.3)].

8.3 Females and Males of Reproductive Potential

ZIIHERA can cause fetal harm when administered to a pregnant woman [see Warnings and Precautions (5.1), Use in Specific Populations (8.1)].

Pregnancy Testing

Verify the pregnancy status of females of reproductive potential prior to the initiation of ZIIHERA [see Use in Specific Populations (8.1)].

Contraception

Females

ZIIHERA can cause embryo-fetal harm when administered during pregnancy. Advise females of reproductive potential to use effective contraception during treatment with ZIIHERA and for 4 months following the last dose of ZIIHERA.

8.4 Pediatric Use

Safety and efficacy of ZIIHERA have not been established in pediatric patients.

8.5 Geriatric Use

Of the 80 patients who received ZIIHERA for unresectable or metastatic biliary tract cancer in HERIZON‑BTC‑01, there were 39 (49%) patients 65 years of age and older. Thirty‑seven (46%) were aged 65‑74 years old and 2 (3%) were aged 75 years or older [see Clinical Studies (14)].

No overall differences in safety or effectiveness were observed between these patients and younger adult patients.

11 DESCRIPTION

Zanidatamab‑hrii is a humanized, IgG-like, bispecific HER2-directed antibody. Zanidatamab‑hrii is produced in Chinese hamster ovary cells via recombinant DNA technology and has a molecular weight of 124.8 kDa.

ZIIHERA (zanidatamab‑hrii) for injection is supplied as a sterile, preservative free, white lyophilized powder that requires reconstitution and dilution for intravenous use. Each single-dose vial of reconstituted product contains 300 mg of zanidatamab‑hrii and the inactive ingredients: polysorbate 20 (0.63 mg), sodium succinate (4.3 mg), succinic acid (4.3 mg), and sucrose (567 mg). Following reconstitution with 5.7 mL Sterile Water for Injection, a solution containing 50 mg/mL zanidatamab‑hrii is produced with a deliverable volume of 6 mL, with pH of 4.6. The resulting solution is diluted and administered by intravenous infusion.

12 CLINICAL PHARMACOLOGY

12.1 Mechanism of Action

Zanidatamab‑hrii is a bispecific HER2-directed antibody that binds to two extracellular sites on HER2. Binding of zanidatamab‑hrii with HER2 results in internalization leading to a reduction of the receptor on the tumor cell surface. Zanidatamab‑hrii induces complement-dependent cytotoxicity (CDC), antibody-dependent cellular cytotoxicity (ADCC) and antibody-dependent cellular phagocytosis (ADCP). These mechanisms result in tumor growth inhibition and cell death in vitro and in vivo.

12.2 Pharmacodynamics

Zanidatamab‑hrii exposure-response relationships and the time course of the pharmacodynamic response are unknown.

Cardiac Electrophysiology

A mean increase in the QTc interval > 20 ms was not observed at the recommended approved dosage.

12.3 Pharmacokinetics

Zanidatamab‑hrii PK parameters are presented as means (percent coefficient of variation) following administration of ZIIHERA 20 mg/kg every 2 weeks after the 7th or later dose unless otherwise indicated.

Zanidatamab‑hrii maximum concentration (Cmax) is 600 (22.2) µg/mL, the lowest measured concentration (Ctrough) is 178 (29.6) µg/mL, and total systemic exposure (AUC0-336h) is 3,976 (22.5) days*µg/mL following administration of ZIIHERA. The Cmax of zanidatamab‑hrii is dose proportional and the total systemic exposure (AUC0-inf) of zanidatamab‑hrii is greater than dose proportional with increasing doses. The mean Ctrough accumulation ratio of zanidatamab‑hrii is approximately 2.4.

Distribution

The volume of distribution of zanidatamab‑hrii is approximately 7.5 (33) L based on the population pharmacokinetic analysis.

Elimination

The estimated half-life (t1/2) of zanidatamab‑hrii is approximately 21 days with an associated clearance (CL) of 0.012 L/h (27.9) based on the population pharmacokinetic analysis.

Metabolism

Zanidatamab‑hrii is expected to be metabolized into small peptides by catabolic pathways.

Specific Populations

No clinically significant differences in the pharmacokinetics of zanidatamab-hrii were observed based on age (24 to 88 years), sex, race (White and Asian), mild and moderate renal impairment (eGFR 30 to 89 mL/min estimated using the CKD‑EPI), mild hepatic impairment (total bilirubin ≤ upper limit of normal (ULN) and AST > ULN or total bilirubin between 1 and 1.5 times ULN and any AST), or body weight (35 kg to 128 kg).

The effect of severe renal impairment (eGFR 15 to 29 mL/min), end-stage renal disease (eGFR < 15 mL/min) with or without hemodialysis, and moderate (total bilirubin > 1.5 to ≤ 3 ULN and any AST) or severe (total bilirubin > 3 ULN and any AST) hepatic impairment on the pharmacokinetics of zanidatamab‑hrii is unknown.

12.6 Immunogenicity

There is insufficient information to characterize the anti-drug antibody response to zanidatamab‑hrii and the effects of anti-drug antibodies on pharmacokinetics, pharmacodynamics, safety, or effectiveness of zanidatamab‑hrii.

13 NONCLINICAL TOXICOLOGY

13.1 Carcinogenesis, Mutagenesis, Impairment of Fertility

Studies have not been conducted to evaluate the carcinogenic or mutagenic potential of zanidatamab‑hrii.

Fertility studies with zanidatamab‑hrii have not been conducted.

14 CLINICAL STUDIES

HER2-positive (IHC 3+) Biliary Tract Cancer (BTC)

The efficacy of ZIIHERA was evaluated in 62 patients with HER2-positive (IHC 3+ by central assessment) BTC in Cohort 1 of HERIZON‑BTC‑01 (NCT04466891), an open-label, multicenter, single arm trial in patients with unresectable or metastatic disease. Patients were required to have received at least one prior gemcitabine-containing systemic chemotherapy regimen in the advanced disease setting and adequate cardiac function (defined as LVEF ≥ 50%).

Patients received ZIIHERA 20 mg/kg intravenously every 2 weeks. ZIIHERA was administered until disease progression or unacceptable toxicity. The major efficacy outcome measures were objective response rate (ORR) and duration of response (DOR) as determined by an independent central review (ICR) according to Response Evaluation Criteria in Solid Tumors (RECIST) v1.1.

The median age was 64 years (range: 38 to 79 years), 47% of patients were age 65 or older; 55% were female; 61% were Asian, 31% were White, 2% were American Indian or Alaskan Native and for 6% race was unknown or not reported; 89% were Non-Hispanic or Latino, 8% Hispanic/Latino, and for 3% ethnicity was unknown or not reported. All patients had a baseline Eastern Cooperative Oncology Group (ECOG) performance status of 0 (32%) or 1 (68%). Fifty-three percent of patients had gallbladder cancer, 27% had intrahepatic cholangiocarcinoma, and 19% had extrahepatic cholangiocarcinoma. All patients received at least 1 prior line of gemcitabine-based therapy, 31% had 2 prior lines of therapy, and 10% had 3 or more prior lines of therapy for unresectable or metastatic disease.

Efficacy results are summarized in Table 5.

Table 5 Efficacy Results in HERIZON-BTC-01
Efficacy Parameter* | ZIIHERA (N=62)
Objective Response Rate (95% CI) | 52% (39, 65)
Complete response, n (%) | 2 (3.2)
Partial response, n (%) | 30 (48)
Duration of Response (DOR) | N=32
Median†, months (95% CI) | 14.9 (7.4, NE)
DOR ≥ 6 months, n (%) ‡ | (19 59)
DOR ≥ 12 months, n (%) ‡ | 14 (44)

*Assessed by independent central review

† Based on Kaplan-Meier estimate

‡ Based on observed duration of response

NE = not estimable

16 HOW SUPPLIED/STORAGE AND HANDLING

ZIIHERA is supplied as a sterile, preservative free, white lyophilized powder in a single-dose vial. Each single-dose vial (NDC 68727‑950‑01) contains 300 mg zanidatamab‑hrii. Each carton of ZIIHERA (NDC 68727‑950‑02) contains 2 single-dose vials.

Store in a refrigerator at 2ºC to 8ºC (36ºF to 46ºF) in the original carton until time of reconstitution. Do not freeze.

17 PATIENT COUNSELING INFORMATION

Advise the patient to read the FDA-approved patient labeling (Patient Information).

Embryo-Fetal Toxicity

Advise female patients of the potential risk to a fetus. Advise female patients to contact their healthcare provider with a known or suspected pregnancy [see Warnings and Precautions (5.1), Use in Specific Populations (8.1)].

Advise females of reproductive potential to use effective contraception during treatment with ZIIHERA and for 4 months following the last dose [see Warnings and Precautions (5.1), Use in Specific Populations (8.3)].

Left Ventricular Dysfunction

Advise patients that ZIIHERA can cause cardiac dysfunction and to contact a healthcare provider immediately for signs and symptoms of cardiac dysfunction [see Warnings and Precautions (5.2)].

Infusion-Related Reactions

Advise patients of the risk of infusion-related reactions and to inform a healthcare provider immediately for symptoms of an infusion-related reaction [see Warnings and Precautions (5.3)].

Diarrhea

Advise patients that ZIIHERA can cause diarrhea, which may be severe. Instruct patients how to manage diarrhea, and to contact their healthcare provider for sustained diarrhea that does not respond to supportive care [see Dosage and Administration (2.4), Warnings and Precautions (5.4)].

Distributed by:
Jazz Pharmaceuticals, Inc.
Palo Alto, CA 94306

Manufactured by:
Jazz Pharmaceuticals Ireland Limited
Fifth Floor, Waterloo Exchange
Waterloo Road, Dublin 4
Dublin, Ireland
D04 E5W7

U.S. License No. 2167

PATIENT INFORMATION
ZIIHERA (zye HAYR rah)
(zanidatamab-hrii)
for injection, for intravenous use

What is the most important information I should know about ZIIHERA?

ZIIHERA can cause serious side effects, including:

- harm to your unborn baby. Tell your healthcare provider right away if you become pregnant or think you may be pregnant during treatment with ZIIHERA.
  - If you are able to become pregnant, your healthcare provider should do a pregnancy test before you start treatment with ZIIHERA.
  - Females who are able to become pregnant should use birth control (contraception) during treatment with ZIIHERA and for 4 months after the last dose.

See “What are the possible side effects of ZIIHERA?” for more information about side effects.

What is ZIIHERA?

ZIIHERA is a prescription medicine used to treat adults who have a type of bile duct (cholangiocarcinoma) or gallbladder cancer called biliary tract cancer (BTC), that is human epidermal growth factor receptor 2 (HER2)-positive (IHC 3+). ZIIHERA may be used when your BTC:

  - was previously treated;
  - cannot be removed by surgery or has spread to other parts of your body (metastatic).

Your healthcare provider will perform a test to make sure ZIIHERA is right for you.

It is not known if ZIIHERA is safe and effective in children.

Before receiving ZIIHERA, tell your healthcare provider about all of your medical conditions, including if you:

- have or have had any heart problems
- are breastfeeding or plan to breastfeed. It is not known if ZIIHERA passes into your breastmilk. Talk to your healthcare provider about the best way to feed your baby if you receive treatment with ZIIHERA.

Tell your healthcare provider about all the medicines you take, including prescription and over-the-counter medicines, vitamins, and herbal supplements.

How should I receive ZIIHERA?

- ZIIHERA is given through a vein by an intravenous (IV) infusion over 120 to 150 minutes for your first and second infusions. If you tolerate the first and second infusions well, your third and fourth infusions may be given to you over 90 minutes. Each additional infusion may be given to you over 60 minutes.
- ZIIHERA is given every 2 weeks.
- Your healthcare provider:
  - will give you medicines 30 to 60 minutes before each treatment to help prevent infusion-related reactions or make them less severe
  - may slow down, temporarily stop, or permanently stop your treatment with ZIIHERA if you have certain side effects
  - may do certain tests to check you for some side effects
  - will decide how many treatments you need
- If you miss a dose, call your healthcare provider as soon as possible to reschedule your appointment.

What are the possible side effects of ZIIHERA?

ZIIHERA can cause serious side effects, including:

- See “What is the most important information I should know about ZIIHERA?”
- Heart problems that may affect how well your heart pumps blood. Your healthcare provider will check your heart function before and during treatment with ZIIHERA. Call your healthcare provider right away if you get any of the following signs and symptoms of a heart problem:
  - new or worsening shortness of breath
  - feeling more tired than usual
  - swelling of your ankles or feet
  - loss of consciousness
  - irregular heartbeat
  - sudden weight gain
  - dizziness or feeling light-headed
- Infusion-related reactions, a common side effect that can happen during treatment with ZIIHERA. Your healthcare provider will check for side effects during your infusions. Tell your healthcare provider right away if you get any of the following symptoms during or after your infusions of ZIIHERA:
  - shortness of breath or trouble breathing
  - fever
  - chills
  - rash
  - flushing
  - nausea or vomiting
  - dizziness or feeling lightheaded
  - chest discomfort
- Diarrhea, a common side effect during treatment with ZIIHERA that may be severe. Your healthcare provider may prescribe an antidiarrheal medicine or other treatment, as needed.

Other common side effects of ZIIHERA include stomach pain and feeling tired.

Tell your healthcare provider if you have any side effect that bothers you or that does not go away.

These are not all of the possible side effects of ZIIHERA.

Call your doctor for medical advice about side effects. You may report side effects to FDA at 1‑800‑FDA‑1088.

General information about the safe and effective use of ZIIHERA.

Medicines are sometimes prescribed for purposes other than those listed in a Patient Information leaflet. You can ask your pharmacist or healthcare provider for information about ZIIHERA that is written for health professionals.

What are the ingredients in ZIIHERA?

Active ingredient: zanidatamab-hrii
Inactive ingredients: polysorbate 20, sodium succinate, succinic acid, and sucrose

Distributed by:
Jazz Pharmaceuticals, Inc.
Palo Alto, CA 94306

Manufactured by:
Jazz Pharmaceuticals Ireland Limited
Fifth Floor, Waterloo Exchange
Waterloo Road, Dublin 4
Dublin, Ireland
D04 E5W7

U.S. License No. 2167

For more information, go to www.ZIIHERA.com or call 1‑800‑520‑5568.

This Patient Information has been approved by the U.S. Food and Drug Administration. | Revised: 7/2025